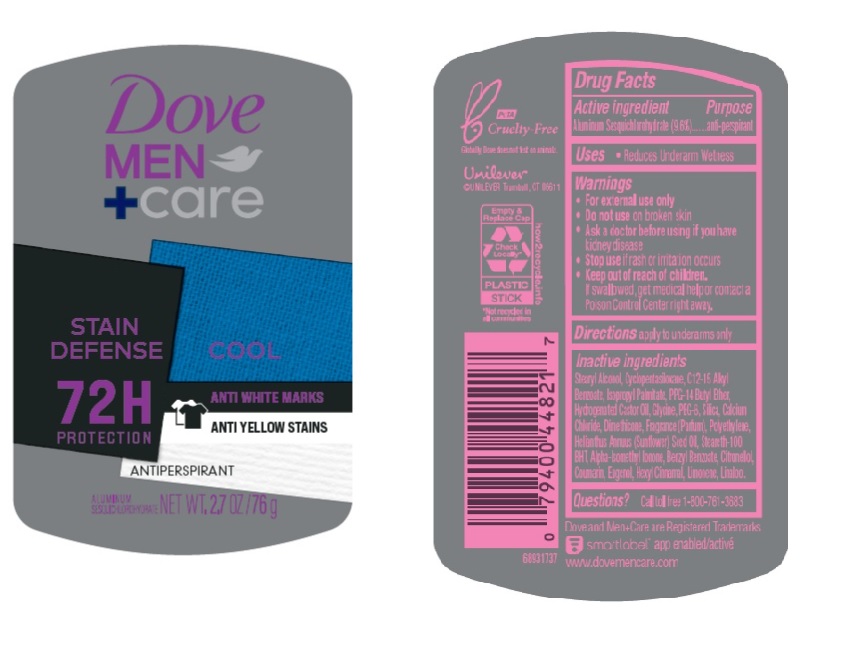 DRUG LABEL: Dove Men plus Care
NDC: 64942-2013 | Form: STICK
Manufacturer: Conopco Inc. d/b/a/ Unilever
Category: otc | Type: HUMAN OTC DRUG LABEL
Date: 20241106

ACTIVE INGREDIENTS: ALUMINUM SESQUICHLOROHYDRATE 12.8 g/100 g
INACTIVE INGREDIENTS: EUGENOL; GLYCINE; CALCIUM CHLORIDE; COUMARIN; .ALPHA.-HEXYLCINNAMALDEHYDE; HIGH DENSITY POLYETHYLENE; CYCLOMETHICONE 5; HYDROGENATED CASTOR OIL; BUTYLATED HYDROXYTOLUENE; PPG-14 BUTYL ETHER; STEARYL ALCOHOL; SUNFLOWER OIL; SILICON DIOXIDE; ALKYL (C12-15) BENZOATE; DIMETHICONE; STEARETH-100; POLYETHYLENE GLYCOL 400; ISOPROPYL PALMITATE; ISOMETHYL-.ALPHA.-IONONE; .BETA.-CITRONELLOL, (R)-; LINALOOL, (+/-)-; LIMONENE, (+)-; BENZYL BENZOATE

Dove Men + Care Stain Defense 72H Antiperspirant

DOVE MEN + CARE STAIN DEFENSE 72H ANTIPERSPIRANT - aluminum sesquichlorohydrate stick

D

Drug Facts

Active ingredient

Aluminum Sesquichlorohydrate (9.6)

Purpose

antiperspirant

Uses

Reduces underarm wetness

Warnings

• For external use only
• Do not use on broken skin
• Ask a doctor before using if you have kidney disease
• Stop use if rash or irritation occurs

• Keep out of reach of children.

If swallowed, get medical help or contact a Poison Control Center right away.

Directions

apply to underarms only

Inactive ingredients

Stearyl Alcohol, Cyclopentasiloxane, C12-15 Alkyl Benzoate, Isopropyl Palmitate, PPG-14 Butyl Ether, Hydrogenated Castor Oil, Glycine, PEG-8, Silica, Calcium Chloride, Dimethicone, Fragrance (Parfum), Polyethylene, Helianthus Annuus (Sunflower) Seed Oil, Steareth-100, BHT, Alpha-IsomethylIonone, Benzyl Benzoate, Citronellol, Coumarin, Eugenol, Hexyl Cinnamal, Limonene, Linalool.

Questions?

Call toll-free 1-800-761-3683